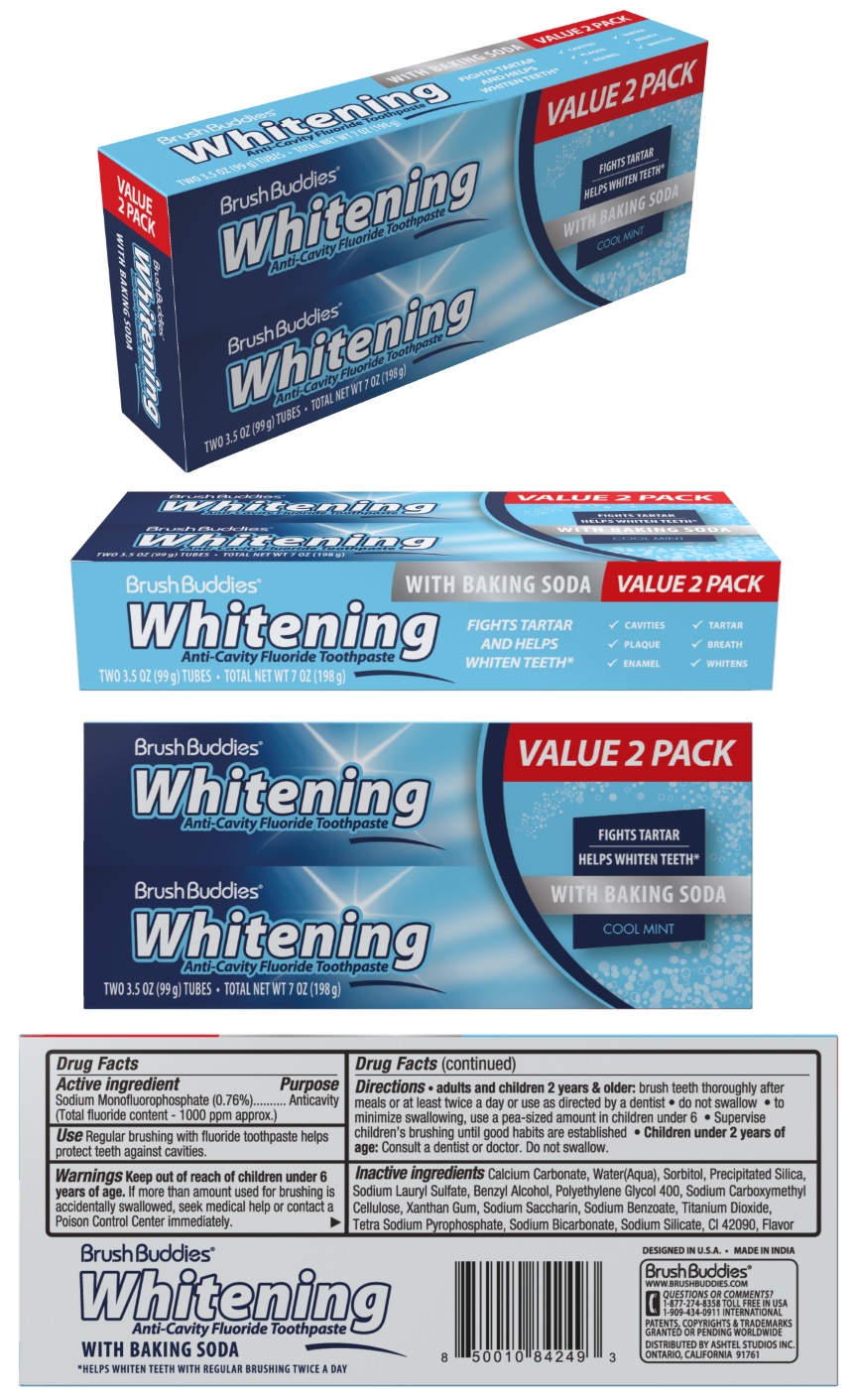 DRUG LABEL: Brush Buddies Value 2 pack Whitening
NDC: 70108-030 | Form: PASTE, DENTIFRICE
Manufacturer: Ashtel Studios, Inc
Category: otc | Type: HUMAN OTC DRUG LABEL
Date: 20250430

ACTIVE INGREDIENTS: SODIUM MONOFLUOROPHOSPHATE 0.76 g/100 g
INACTIVE INGREDIENTS: CALCIUM CARBONATE; WATER; SORBITOL; SILICON DIOXIDE; SODIUM LAURYL SULFATE; BENZYL ALCOHOL; POLYETHYLENE GLYCOL 400; CARBOXYMETHYLCELLULOSE SODIUM, UNSPECIFIED; XANTHAN GUM; SACCHARIN SODIUM; SODIUM BENZOATE; TITANIUM DIOXIDE; SODIUM PYROPHOSPHATE; SODIUM BICARBONATE; SODIUM SILICATE; FD&C BLUE NO. 1

Brush Buddies® Whitening Anti-Cavity Fluoride Toothpaste

Active ingredient

Sodium Monofluorophosphate (0.76%)
(Total fluoride content - 1000 ppm approx.)

Purpose

Anticavity

Use

Regular brushing with fluoride toothpaste helps protect teeth against cavities.

Warnings

Keep out of reach of children under 6 years of age. If more than amount used for brushing is accidentally swallowed, seek medical help or contact a Poison Control Center immediately.

Directions

• adults and children 2 years & older: brush teeth thoroughly after meals or at least twice a day or use as directed by a dentist do not swallow • to minimize swallowing, use a pea-sized amount in children under 6 • Supervise children's brushing until good habits are established • Children under 2 years of age: Consult a dentist or doctor. Do not swallow.

Inactive ingredients

Calcium Carbonate, Water(Aqua), Sorbitol, Precipitated Silica, Sodium Lauryl Sulfate, Benzyl Alcohol, Polyethylene Glycol 400, Sodium Carboxymethyl Cellulose, Xanthan Gum, Sodium Saccharin, Sodium Benzoate, Titanium Dioxide, Tetra Sodium Pyrophosphate, Sodium Bicarbonate, Sodium Silicate, CI 42090, Flavor

FIGHTS TARTAR AND HELPS WHITEN TEETH*

WITH BAKING SODA

COOL MINT

√ CAVITIES √ TARTAR

√ PLAQUE √ BREATH

√ ENAMEL √ WHITENS

*HELPS WHITEN TEETH WITH REGULAR BRUSHING TWICE A DAY

DESIGNED IN U.S.A. • MADE IN INDIA

WWW.BRUSHBUDDIES.COM

QUESTIONS OR COMMENTS?
1-877-274-8358 TOLL FREE IN USA
1-909-434-0911 INTERNATIONAL

PATENTS, COPYRIGHTS & TRADEMARKS GRANTED OR PENDING WORLDWIDE

DISTRIBUTED BY ASHTEL STUDIOS INC.
ONTARIO, CALIFORNIA 91761